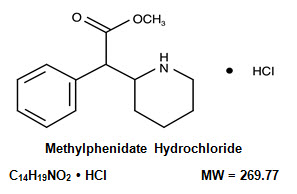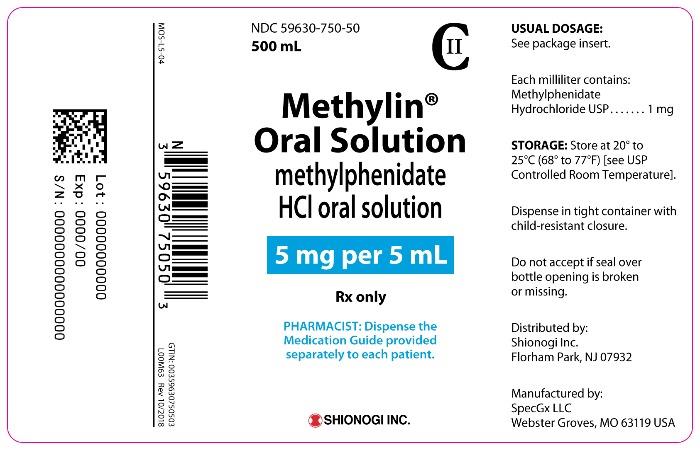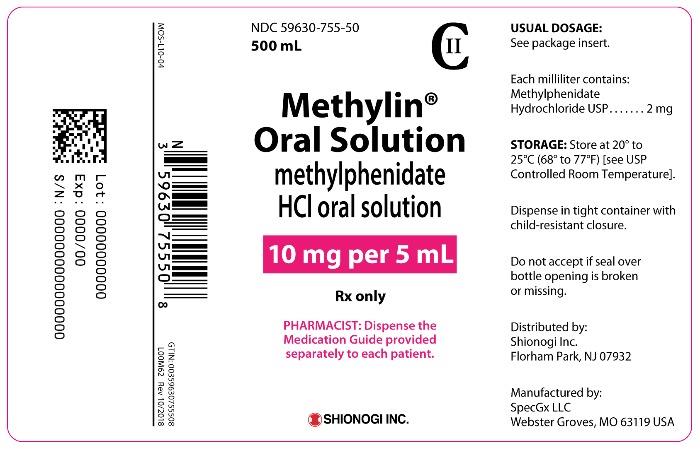 DRUG LABEL: Methylin
NDC: 59630-750 | Form: SOLUTION
Manufacturer: SHIONOGI INC.
Category: prescription | Type: HUMAN PRESCRIPTION DRUG LABEL
Date: 20231101
DEA Schedule: CII

ACTIVE INGREDIENTS: METHYLPHENIDATE HYDROCHLORIDE 5 mg/5 mL
INACTIVE INGREDIENTS: ANHYDROUS CITRIC ACID; GLYCERIN; POLYETHYLENE GLYCOL 1450; WATER

HIGHLIGHTS OF PRESCRIBING INFORMATION

These highlights do not include all the information needed to use METHYLIN® safely and effectively. See full prescribing information for METHYLIN®.
METHYLIN® (methylphenidate hydrochloride) oral solution, CII
Initial U.S. Approval: 1955

WARNING: ABUSE, MISUSE, AND ADDICTION

See full prescribing information for complete boxed warning.

Methylin has a high potential for abuse and misuse, which can lead to the development of a substance use disorder, including addiction. Misuse and abuse of CNS stimulants, including Methylin, can result in overdose and death (5.1, 9.2, 10):

- Before prescribing Methylin, assess each patient’s risk for abuse, misuse, and addiction.
- Educate patients and their families about these risks, proper storage of the drug, and proper disposal of any unused drug.
- Throughout treatment, reassess each patient’s risk and frequently monitor for signs and symptoms of abuse, misuse, and addiction.

RECENT MAJOR CHANGES

Boxed Warning | 10/2023
Dosage and Administration (2.1, 2.2, 2.3) | 10/2023
Warnings and Precautions (5.1, 5.2, 5.8, 5.9, 5.10) | 10/2023

1 INDICATIONS AND USAGE

Methylin is a central nervous system (CNS) stimulant indicated for the treatment of:

- Attention Deficit Hyperactivity Disorder (ADHD) in adults and pediatric patients 6 years of age and older (1)
- Narcolepsy (1)

2 DOSAGE AND ADMINISTRATION

- Pediatric patients 6 years and older: Starting dose is 5 mg twice daily (before breakfast and lunch); increase the dose 5 mg to 10 mg weekly; daily dosage above 60 mg is not recommended. (2.2)
- Adults: Administer in divided doses 2 or 3 times daily, preferably 30 to 45 minutes before meals. Average dosage is 20 to 30 mg daily. Maximum recommended daily dosage is 60 mg. (2)

3 DOSAGE FORMS AND STRENGTHS

Oral solution: 5 mg per 5 mL and 10 mg per 5 mL. (3)

4 CONTRAINDICATIONS

- Known hypersensitivity to methylphenidate or other components of Methylin (4)
- Concurrent treatment with a monoamine oxidase inhibitor (MAOI), or use of an MAOI within the preceding 14 days (4)

5 WARNINGS AND PRECAUTIONS

- Risks to Patients with Serious Cardiac Disease: Avoid use in patients with known structural cardiac abnormalities, cardiomyopathy, serious cardiac arrhythmias, coronary artery disease, or other serious cardiac disease. (5.2)
- Increased Blood Pressure and Heart Rate: Monitor blood pressure and pulse. (5.3)
- Psychiatric Adverse Reactions: Prior to initiating Methylin, screen patients for risk factors for developing a manic episode. If new psychotic or manic symptoms occur, consider discontinuing Methylin. (5.4)
- Priapism: If abnormally sustained or frequent and painful erections occur, patients should seek immediate medical attention. (5.5)
- Peripheral Vasculopathy, Including Raynaud’s Phenomenon: Careful observation for digital changes is necessary during Methylin treatment. Further clinical evaluation (e.g., rheumatology referral) may be appropriate for patients who develop signs or symptoms of peripheral vasculopathy. (5.6)
- Long-Term Suppression of Growth in Pediatric Patients: Closely monitor (height and weight) in pediatric patients. Pediatric patients not growing or gaining height or weight as expected may need to have their treatment interrupted. (5.7)
- Acute Angle Closure Glaucoma: Methylin-treated patients considered at risk for acute angle closure glaucoma (e.g., patients with significant hyperopia) should be evaluated by an ophthalmologist. (5.8)
- Increased Intraocular Pressure (IOP) and Glaucoma: Prescribe Methylin to patients with open-angle glaucoma or abnormally increased IOP only if the benefit of treatment is considered to outweigh the risk. Closely monitor patients with a history of increased IOP or open-angle glaucoma. (5.9)
- Motor and Verbal Tics, and Worsening of Tourette’s Syndrome: Before initiating Methylin, assess the family history and clinically evaluate patients for tics or Tourette’s syndrome. Regularly monitor patients for the emergence or worsening of tics or Tourette’s syndrome. Discontinue treatment if clinically appropriate. (5.10)

6 ADVERSE REACTIONS

Common adverse reactions: tachycardia, palpitations, headache, insomnia, anxiety, hyperhidrosis, weight loss, decreased appetite, dry mouth, nausea, and abdominal pain. (6)

To report SUSPECTED ADVERSE REACTIONS contact Shionogi Inc. at 1-800-849-9707 or FDA at 1-800-FDA-1088 or www.fda.gov/medwatch.

7 DRUG INTERACTIONS

- Antihypertensive Drugs: Monitor blood pressure. Adjust dosage of antihypertensive drug as needed. (7.1)

FULL PRESCRIBING INFORMATION

WARNING: ABUSE, MISUSE, AND ADDICTION

Methylin has a high potential for abuse and misuse, which can lead to the development of a substance use disorder, including addiction. Misuse and abuse of CNS stimulants, including Methylin, can result in overdose and death [see Overdosage (10)], and this risk is increased with higher doses or unapproved methods of administration, such as snorting or injection.

Before prescribing Methylin, assess each patient’s risk for abuse, misuse, and addiction. Educate patients and their families about these risks, proper storage of the drug, and proper disposal of any unused drug. Throughout Methylin treatment, reassess each patient’s risk of abuse, misuse, and addiction and frequently monitor for signs and symptoms of abuse, misuse, and addiction [see Warnings and Precautions (5.1) and Drug Abuse and Dependence (9.2)].

RECENT MAJOR CHANGES

Boxed Warning | 05/2023
Dosage and Administration (2.1, 2.2, 2.3) | 05/2023
Warnings and Precautions (5.1, 5.2, 5.8, 5.9, 5.10) | 05/2023

1 INDICATIONS AND USAGE

Methylin is indicated for the treatment of:

- Attention Deficit Hyperactivity Disorder (ADHD) in adults and pediatric patients 6 years of age and older
- Narcolepsy

2 DOSAGE AND ADMINISTRATION

2.1 Pretreatment Screening

Prior to treating patients with Methylin, assess:

- for the presence of cardiac disease (i.e., perform a careful history, family history of sudden death or ventricular arrhythmia, and physical exam) [see Warnings and Precautions (5.2)].
- the family history and clinically evaluate patients for motor or verbal tics or Tourette’s syndrome [see Warnings and Precautions (5.10)].

2.2 General Dosing Information

Pediatric Patients 6 years of Age and Older
The recommended starting dosage is 5 mg orally twice daily before breakfast and lunch (preferably 30 to 45 minutes before meals). Increase the dosage gradually, in increments of 5 mg to 10 mg weekly. Daily dosage above 60 mg is not recommended.

Adults
Administer orally in divided doses 2 or 3 times daily, preferably 30 to 45 minutes before meals. The maximum recommended daily dose is 60 mg. The average dosage is 20 to 30 mg daily. For adult patients who are unable to sleep if medication is taken late in the day, administer the last dose before 6 p.m.

2.3 Dosage Reduction and Discontinuation

If paradoxical aggravation of symptoms or other adverse reactions occur, reduce dosage, or, if necessary, discontinue Methylin. If improvement is not observed after appropriate dosage adjustment over a one-month period, discontinue Methylin.

3 DOSAGE FORMS AND STRENGTHS

Methylin oral solution is a colorless, grape flavored liquid available in a 500 mL bottle in the following strengths:

- 5 mg per 5 mL
- 10 mg per 5 mL

4 CONTRAINDICATIONS

Methylin is contraindicated in patients:

- with known hypersensitivity to methylphenidate or other components of Methylin. Hypersensitivity reactions such as angioedema and anaphylactic reactions have been reported in patients treated with methylphenidate [see Adverse Reactions (6)].
- receiving concomitant treatment with monoamine oxidase inhibitors (MAOIs), or within 14 days following discontinuation of treatment with an MAOI, because of the risk of hypertensive crises [see Drug Interactions (7)].

5 WARNINGS AND PRECAUTIONS

5.1 Abuse, Misuse, and Addiction

Methylin has a high potential for abuse and misuse. The use of Methylin exposes individuals to the risks of abuse and misuse, which can lead to the development of a substance use disorder, including addiction. Methylin can be diverted for non-medical use into illicit channels or distribution [see Drug Abuse and Dependence (9.2)]. Misuse and abuse of CNS stimulants, including Methylin, can result in overdose and death [see Overdosage (10)], and this risk is increased with higher doses or unapproved methods of administration, such as snorting or injection.

Before prescribing Methylin, assess each patient’s risk for abuse, misuse, and addiction. Educate patients and their families about these risks and proper disposal of any unused drug. Advise patients to store Methylin in a safe place, preferably locked, and instruct patients to not give Methylin to anyone else. Throughout Methylin treatment, reassess each patient’s risk of abuse, misuse, and addiction and frequently monitor for signs and symptoms of abuse, misuse, and addiction.

5.2 Risks to Patients with Serious Cardiac Disease

Sudden death has been reported in patients with structural cardiac abnormalities or other serious cardiac disease who were treated with CNS stimulants at the recommended ADHD dosage.

Avoid Methylin use in patients with known structural cardiac abnormalities, cardiomyopathy, serious cardiac arrythmia, coronary artery disease, or other serious cardiac disease.

5.3 Increased Blood Pressure and Heart Rate

CNS stimulants cause an increase in blood pressure (mean increase approximately 2 to 4 mmHg) and heart rate (mean increase approximately 3 to 6 bpm). Some patients may have larger increases.

Monitor all Methylin-treated patients for hypertension and tachycardia.

5.4 Psychiatric Adverse Reactions

Exacerbation of Pre-Existing Psychosis
CNS stimulants may exacerbate symptoms of behavior disturbance and thought disorder in patients with a pre-existing psychotic disorder.

Induction of a Manic Episode in Patients with Bipolar Illness
CNS stimulants may induce a manic or mixed mood episode in patients. Prior to initiating Methylin treatment, screen patients for risk factors for developing a manic episode (e.g., comorbid or history of depressive symptoms or a family history of suicide, bipolar disorder, or depression).

New Psychotic or Manic Symptoms
CNS stimulants, at the recommended dosages, may cause psychotic or manic symptoms (e.g., hallucinations, delusional thinking, or mania) in patients without a prior history of psychotic illness or mania. In a pooled analysis of multiple short-term, placebo-controlled studies of CNS stimulants, psychotic or manic symptoms occurred in approximately 0.1% of CNS stimulant-treated patients, compared with 0% of placebo-treated patients. If such symptoms occur, consider discontinuing Methylin.

5.5 Priapism

Prolonged and painful erections, sometimes requiring surgical intervention, have been reported with methylphenidate use in both adult and pediatric male patients. Although priapism was not reported with methylphenidate initiation, it developed after some time on methylphenidate, often subsequent to an increase in dosage. Priapism also occurred during methylphenidate withdrawal (drug holidays or during discontinuation).

Methylin-treated patients who develop abnormally sustained or frequent and painful erections should seek immediate medical attention.

5.6 Peripheral Vasculopathy, Including Raynaud’s Phenomenon

CNS stimulants, including Methylin, used to treat ADHD are associated with peripheral vasculopathy, including Raynaud’s phenomenon. Signs and symptoms are usually intermittent and mild; however, sequelae have included digital ulceration and/or soft tissue breakdown. Effects of peripheral vasculopathy, including Raynaud’s phenomenon, were observed in postmarketing reports and at the therapeutic dosages of CNS stimulants in all age groups throughout the course of treatment. Signs and symptoms generally improved after dosage reduction or discontinuation of the CNS stimulant.

Careful observation for digital changes is necessary during Methylin treatment. Further clinical evaluation (e.g., rheumatology referral) may be appropriate for Methylin-treated patients who develop signs or symptoms of peripheral vasculopathy.

5.7 Long-Term Suppression of Growth in Pediatric Patients

CNS stimulants have been associated with weight loss and slowing of growth rate in pediatric patients.

Careful follow-up of weight and height in children ages 7 to 10 years who were randomized to either methylphenidate or non-medication treatment groups over 14 months, as well as in naturalistic subgroups of newly methylphenidate-treated and non-medication-treated pediatric patients over 36 months (to the ages of 10 to 13 years), suggests that pediatric patients who received methylphenidate for 7 days per week throughout the year had a temporary slowing in growth rate (on average, a total of about 2 cm less growth in height and 2.7 kg less growth in weight over 3 years), without evidence of growth rebound during this development period.

Closely monitor growth (weight and height) in Methylin-treated pediatric patients. Pediatric patients who are not growing or gaining height or weight as expected may need to have their treatment interrupted. The safety and effectiveness of Methylin have not been established in pediatric patient less than 6 years of age.

5.8 Acute Angle Closure Glaucoma

There have been reports of angle closure glaucoma associated with methylphenidate treatment. Although the mechanism is not clear, Methylin-treated patients considered at risk for acute angle closure glaucoma (e.g., patients with significant hyperopia) should be evaluated by an ophthalmologist.

5.9 Increased Intraocular Pressure and Glaucoma

There have been reports of an elevation of intraocular pressure (IOP) associated with methylphenidate treatment [see Adverse Reactions (6.2)].

Prescribe Methylin to patients with open-angle glaucoma or abnormally increased IOP only if the benefit of treatment is considered to outweigh the risk. Closely monitor Methylin-treated patients with a history of abnormally increased IOP or open-angle glaucoma.

5.10 Motor and Verbal Tics, and Worsening of Tourette’s Syndrome

CNS stimulants, including methylphenidate, have been associated with the onset or exacerbation of motor and verbal tics. Worsening of Tourette’s syndrome has also been reported [see Adverse Reactions (6.2)].

Before initiating Methylin, assess the family history and clinically evaluate patients for tics or Tourette’s syndrome. Regularly monitor Methylin-treated patients for the emergence or worsening of tics or Tourette’s syndrome, and discontinue treatment if clinically appropriate.

6 ADVERSE REACTIONS

The following adverse reactions are discussed in more detail in other sections of the labeling:

- Abuse, misuse, and addiction [see Warnings and Precautions (5.1), Drug Abuse and Dependence (9.2, 9.3)]

- Known hypersensitivity to methylphenidate or other components of Methylin [see Contraindications (4)]

- Hypertensive crisis when used concomitantly with monoamine oxidase inhibitors [see Contraindications (4), Drug Interactions (7)]

- Risks to patients with serious cardiac disease [see Warnings and Precautions (5.2)]

- Increased blood pressure and heart rate [see Warnings and Precautions (5.3)]

- Psychiatric adverse reactions [see Warnings and Precautions (5.4)]

- Priapism [see Warnings and Precautions (5.5)]

- Peripheral vasculopathy, including Raynaud’s phenomenon [see Warnings and Precautions (5.6)]

- Long-term suppression of growth in pediatric patients [see Warnings and Precautions (5.7)]
- Acute angle closure glaucoma [see Warnings and Precautions (5.8)]
- Increased intraocular pressure and glaucoma [see Warnings and Precautions (5.9)]
- Motor and verbal tics, and worsening of Tourette’s syndrome [see Warnings and Precautions (5.10)]

The following adverse reactions associated with the use of methylphenidate containing products were identified in clinical studies, postmarketing reports, or literature. Because some of these reactions were reported voluntarily from a population of uncertain size, it is not always possible to reliably estimate their frequency or establish a causal relationship to drug exposure.

Infections and infestations: nasopharyngitis

Blood and the lymphatic system disorders: leukopenia, thrombocytopenia, anemia, pancytopenia

Immune system disorders: hypersensitivity reactions, including angioedema and anaphylaxis, auricular swelling, bullous conditions, eruptions, exanthemas

Metabolism and nutrition disorders: decreased appetite, reduced weight gain and suppression of growth during prolonged use in pediatric patients

Psychiatric disorders: insomnia, anxiety, restlessness, agitation, psychosis (sometimes with visual and tactile hallucinations), depressed mood, affect lability, mania, disorientation, libido changes

Nervous system disorders: headache, dizziness, tremor, dyskinesia including choreoatheetoid movements, drowsiness, convulsions, cerebral arteritis and/or occlusion, serotonin syndrome in combination with serotonergic drugs, migraine, motor and verbal tics

Eye disorders: blurred vision, difficulties in visual accommodation, diplopia, mydriasis, increased intraocular pressure

Cardiac disorders: tachycardia, palpitations, increased blood pressure, arrhythmias, angina pectoris, sudden cardiac death, myocardial infarction, bradycardia, extrasystole

Respiratory, thoracic and mediastinal disorders: cough, pharyngolaryngeal pain, dyspnea

Gastrointestinal disorders: dry mouth, nausea, vomiting, abdominal pain, dyspepsia, diarrhea

General disorders: fatigue, hyperpyrexia

Hepatobiliary disorders: abnormal liver function, ranging from transaminase elevation to severe hepatic injury

Skin and subcutaneous tissue disorders: hyperhidrosis, pruritus, urticaria, exfoliative dermatitis, scalp hair loss, erythema multiforme rash, thrombocytopenic purpura angioneurotic edema, erythema, fixed drug eruption

Musculoskeletal and connective tissue disorders: arthralgia, muscle cramps, rhabdomyolysis, myalgia, muscle twitching

Renal and urinary disorders: hematuria

Reproductive system and breast disorders: gynecomastia

Urogenital disorders: priapism

Vascular disorders: peripheral coldness, Raynaud’s phenomenon

Investigations: weight loss

7 DRUG INTERACTIONS

7.1 Clinically Important Drug Interactions with Methylin

Table 1 presents clinically important drug interactions with Methylin.

Table 1: Clinically Important Drug Interactions with Methylin
Monoamine Oxidase Inhibitors (MAOI)
Clinical Impact: | Concomitant use of MAOIs and CNS stimulants, including Methylin, can cause hypertensive crisis. Potential outcomes include death, stroke, myocardial infarction, aortic dissection, ophthalmological complications, eclampsia, pulmonary edema, and renal failure [see Contraindications (4)].
Intervention: | Concomitant use of Methylin with monoamine oxidase inhibitors (MAOIs) or within 14 days after discontinuing MAOI treatment is contraindicated.
Antihypertensive Drugs
Clinical Impact: | Methylin may decrease the effectiveness of drugs used to treat hypertension [see Warnings and Precautions (5.3)].
Intervention: | Monitor blood pressure and adjust the dosage of the antihypertensive drug as needed.
Halogenated Anesthetics
Clinical Impact: | Concomitant use of halogenated anesthetics and Methylin may increase the risk of sudden blood pressure and heart rate increase during surgery.
Intervention: | Avoid use of Methylin in patients being treated with anesthetics on the day of surgery.
Risperidone
Clinical Impact: | Combined use of methylphenidate with risperidone when there is a change, whether an increase or decrease, in dosage of either or both medications, may increase the risk of extrapyramidal symptoms (EPS).
Intervention: | Monitor for signs of EPS.

8 USE IN SPECIFIC POPULATIONS

8.1 Pregnancy

Pregnancy Exposure Registry
There is a pregnancy exposure registry that monitors pregnancy outcomes in women exposed to ADHD medications, including Methylin, during pregnancy. Healthcare providers are encouraged to register patients by calling the National Pregnancy Registry for Psychostimulants at 1-866-961-2388.

Risk Summary
Published studies and postmarketing reports on methylphenidate use during pregnancy have not identified a drug-associated risk of major birth defects, miscarriage or adverse maternal or fetal outcomes. There may be risks to the fetus associated with the use of CNS stimulants use during pregnancy (see Clinical Considerations).

No effects on morphological development were observed in embryo-fetal development studies with oral administration of methylphenidate to pregnant rats and rabbits during organogenesis at doses up to 12 and 19 times, respectively, the maximum recommended human dose (MRHD) of 60 mg/day given to adults on a mg/m^2 basis. However, spina bifida was observed in rabbits at a dose 65 times the MRHD given to adults. A decrease in pup body weight was observed in a pre- and post-natal development study with oral administration of methylphenidate to rats throughout pregnancy and lactation at doses 7 times the MRHD given to adults (see Data).

The estimated background risk of major birth defects and miscarriage for the indicated population is unknown. All pregnancies have a background risk of birth defect, loss, or other adverse outcomes. In the U.S. general population, the estimated background risk of major birth defects and miscarriage in clinically recognized pregnancies is 2% to 4% and 15% to 20%, respectively.

Clinical Considerations
Fetal/Neonatal Adverse Reactions
CNS stimulants, such as Methylin, can cause vasoconstriction and thereby decrease placental perfusion. No fetal and/or neonatal adverse reactions have been reported with the use of therapeutic doses of methylphenidate during pregnancy; however, premature delivery and low birth weight infants have been reported in amphetamine-dependent mothers.

Data
Animal Data
In embryo-fetal development studies conducted in rats and rabbits, methylphenidate was administered orally at doses of up to 75 and 200 mg/kg/day, respectively, during the period of organogenesis. Malformations (increased incidence of fetal spina bifida) were observed in rabbits at the highest dose, which is approximately 65 times the MRHD of 60 mg/day given to adults on a mg/m^2 basis. The no effect level for embryo-fetal development in rabbits was 60 mg/kg/day (19 times the MRHD given to adults on a mg/m^2 basis). There was no evidence of morphological development effects in rats, although increased incidences of fetal skeletal variations were seen at the highest dose level (12 times the MRHD of 60 mg/day given to adults on a mg/m^2 basis), which was also maternally toxic. The no effect level for embryo-fetal development in rats was 25 mg/kg/day (4 times the MRHD on a mg/m^2 basis). When methylphenidate was administered to rats throughout pregnancy and lactation at doses of up to 45 mg/kg/day, offspring body weight gain was decreased at the highest dose (7 times the MRHD of 60 mg/day given to adults on a mg/m^2 basis), but no other effects on postnatal development were observed. The no effect level for pre- and postnatal development in rats was 15 mg/kg/day (~2 times the MRHD given to adults on a mg/m^2 basis).

8.2 Lactation

Risk Summary
Limited published literature, based on milk sampling from seven mothers reports that methylphenidate is present in human milk, which resulted in infant doses of 0.16% to 0.7% of the maternal weight-adjusted dosage and a milk/plasma ratio ranging between 1.1 and 2.7. There are no reports of adverse effects on the breastfed infant and no effects on milk production. Long-term neurodevelopmental effects on infants from stimulant exposure are unknown. The developmental and health benefits of breastfeeding should be considered along with the mother’s clinical need for Methylin and any potential adverse effects on the breastfed infant from Methylin or from the underlying maternal condition.

Clinical Considerations
Monitor breastfeeding infants for adverse reactions, such as agitation, insomnia, anorexia, and reduced weight gain.

8.4 Pediatric Use

The safety and effectiveness of Methylin for the treatment of ADHD have been established in pediatric patients six years of age and older. The safety and effectiveness of Methylin in pediatric patients under six years of age have not been established. The long-term efficacy of methylphenidate in pediatric patients has not been established.

Long-Term Suppression of Growth
Growth should be monitored during treatment with stimulants, including Methylin. Pediatric patients who are not growing or gaining weight as expected may need to have their treatment interrupted [see Warnings and Precautions (5.6)].

Juvenile Animal Toxicity Data
In a study conducted in young rats, methylphenidate was administered orally at doses of up to 100 mg/kg/day for 9 weeks, starting early in the postnatal period (postnatal Day 7) and continuing through sexual maturity (postnatal Week 10). When these animals were tested as adults (postnatal Weeks 13 -14), decreased spontaneous locomotor activity was observed in males and females previously treated with 50 mg/kg/day (approximately 4 times the MRHD of 60 mg/day given to children on a mg/m^2 basis) or greater, and a deficit in the acquisition of a specific learning task was seen in females exposed to the highest dose (8 times the MRHD given to children on a mg/m^2 basis). The no effect level for juvenile neurobehavioral development in rats (5 mg/kg/day) is less than the MRHD given to children on a mg/m^2 basis. The clinical significance of the long-term behavioral effects observed in rats is unknown.

8.5 Geriatric Use

Methylin has not been studied in the geriatric population.

9 DRUG ABUSE AND DEPENDENCE

9.1 Controlled Substance

Methylin contains methylphenidate hydrochloride, a Schedule II controlled substance.

9.2 Abuse

Methylin has a high potential for abuse and misuse which can lead to the development of a substance use disorder, including addiction [see Warnings and Precautions (5.1)]. Methylin can be diverted for non medical use into illicit channels or distribution.

Abuse is the intentional non-therapeutic use of a drug, even once, to achieve a desired psychological or physiological effect. Misuse is the intentional use, for therapeutic purposes, of a drug by an individual in a way other than prescribed by a healthcare provider or for whom it was not prescribed. Drug addiction is a cluster of behavioral, cognitive, and physiological phenomena that may include a strong desire to take the drug, difficulties in controlling drug use (e.g., continuing drug use despite harmful consequences, giving a higher priority to drug use than other activities and obligations), and possible tolerance or physical dependence.

Misuse and abuse of methylphenidate may cause increased heart rate, respiratory rate, or blood pressure; sweating; dilated pupils; hyperactivity; restlessness; insomnia; decreased appetite; loss of coordination; tremors; flushed skin; vomiting; and/or abdominal pain. Anxiety, psychosis, hostility, aggression, and suicidal or homicidal ideation have also been observed with CNS stimulants abuse and/or misuse. Misuse and abuse of CNS stimulants, including Methylin, can result in overdose and death [see Overdosage (10)], and this risk is increased with higher doses and or unapproved methods of administration, such as snorting or injection

9.3 Dependence

Physical Dependence
Methylin may produce physical dependence. Physical dependence is a state that develops as a result of physiological adaptation in response to repeated drug use, manifested by withdrawal signs and symptoms after abrupt discontinuation or a significant dose reduction of a drug.

Withdrawal signs and symptoms after abrupt discontinuation or dose reduction following prolonged use of CNS stimulants including Methylin include dysphoric mood; depression; fatigue; vivid, unpleasant dreams; insomnia or hypersomnia; increased appetite; and psychomotor retardation or agitation.

Tolerance
Methylin may produce tolerance. Tolerance is a physiological state characterized by a reduced response to a drug after repeated administration (i.e., a higher dose of a drug is required to produce the same effect that was once obtained at a lower dose).

10 OVERDOSAGE

Clinical Effects of Overdose
Overdose of CNS stimulants is characterized by the following sympathomimetic effects:

- Cardiovascular effects including tachyarrhythmias, and hypertension or hypotension. Vasospasm, myocardial infarction, or aortic dissection may precipitate sudden cardiac death. Takotsubo cardiomyopathy may develop.
- CNS effects including psychomotor agitation, confusion, and hallucinations. Serotonin syndrome, seizures, cerebral vascular accidents, and coma may occur.
- Life-threatening hyperthermia (temperatures greater than 104°F) and rhabdomyolysis may develop.

Overdose Management
Consider the possibility of multiple drug ingestion. Because methylphenidate has a large volume of distribution and is rapidly metabolized, dialysis is not useful. Consider contacting the Poison Help line (1-800-222-1222) or a medical toxicologist for additional overdose management recommendations.

11 DESCRIPTION

Methylin contains methylphenidate hydrochloride a CNS stimulant. It is available as an oral solution in 5 mg/5 mL and 10 mg/5 mL strengths for oral administration. Chemically, methylphenidate hydrochloride is (d,l (racemic) methyl α-phenyl-2-piperidineacetate hydrochloride and its structural formula is:

Methylphenidate hydrochloride is a white, odorless, fine crystalline powder. Its solutions are acid to litmus. It is freely soluble in water and in methanol, soluble in alcohol, and slightly soluble in chloroform and in acetone.

Each mL of Methylin 5 mg/5 mL contains 1 mg of methylphenidate hydrochloride USP.

Each mL of Methylin 10 mg/5 mL contains 2 mg of methylphenidate hydrochloride USP.

Methylin also contains the following inactive ingredients: citric acid anhydrous, glycerin, N&A grape flavor, PEG 1450, and purified water.

12 CLINICAL PHARMACOLOGY

12.1 Mechanism of Action

Methylphenidate hydrochloride is a central nervous system (CNS) stimulant. The mode of therapeutic action in ADHD is not known.

12.2 Pharmacodynamics

Methylphenidate is a racemic mixture comprised of the d- and l-threo enantiomers. The d-threo enantiomer is more pharmacologically active than the l-threo enantiomer. Methylphenidate blocks the reuptake of norepinephrine and dopamine into the presynaptic neuron and increases the release of these monoamines into the extraneuronal space.

Cardiac Electrophysiology
A formal QT study has not been conducted in subjects taking Methylin.

The effect of dexmethylphenidate, the pharmacologically active d-enantiomer of Methylin, on the QT interval was evaluated in a double-blind, placebo- and open-label active (moxifloxacin)-controlled study following single doses of 40 mg dexmethylphenidate hydrochloride extended-release capsule in 75 healthy volunteers. Electrocardiograms were collected up to 12 hours postdose. Frederica’s method for heart rate correction was employed to derive the corrected QT interval (QTcF). The maximum mean prolongation of QTcF intervals was less than 5 ms, and the upper limit of the 90% confidence interval was below 10 ms for all time-matched comparisons versus placebo. This was below the threshold of clinical concern and there was no evident exposure response relationship.

12.3 Pharmacokinetics

Absorption

Following a single dose administration of 20 mg Methylin and 20 mg tablet of methylphenidate hydrochloride in healthy volunteers under fasted conditions, time to peak plasma concentration (Tmax) of methylphenidate was at 1 to 2 hours after dosing, and:

- The mean peak plasma concentration (Cmax) of methylphenidate was 9.1 ng/mL and 9.8 ng/mL, respectively.
- The mean area under concentration curve (AUC) of methylphenidate was 46.7 hour*ng/mL and 50.0 hour*ng/mL, respectively.

Effect of Food
Ingestion of a high-fat meal with Methylin increased methylphenidate mean Cmax and AUC by about 13% and 25%, respectively. Time to Cmax (Tmax) was delayed by approximately 1 hour.

Distribution
Plasma protein binding is 10% to 33%. The volume of distribution was 2.65 ± 1.11 L/kg for
d-methylphenidate and 1.80 ± 0.91 L/kg for l-methylphenidate.

Elimination
The mean terminal half-life (t½) of methylphenidate was 2.7 hours following administration of 20 mg Methylin Oral Solution. The systemic clearance is 0.40 ± 0.12 L/h/kg for d-methylphenidate and 0.73 ± 0.28 L/h/kg for l-methylphenidate.

Metabolism
Methylphenidate is metabolized primarily by deesterification to alpha-phenyl-piperidine acetic acid (ritalinic acid), which has little or no pharmacologic activity.

Excretion
After oral dosing of radiolabeled methylphenidate in humans, about 90% of the radioactivity was recovered in urine. The main urinary metabolite was ritalinic acid, accounting for approximately 80% of the dose.

Specific Populations
Male and Female Patients, Racial Groups, and Age
The effect of gender, race, and age on the pharmacokinetics of methylphenidate after Methylin administration have not been studied.

Patients with Renal Impairment
Methylin has not been studied in in patients with renal impairment. Since renal clearance is not an important route of methylphenidate clearance, renal impairment is expected to have little effect on the pharmacokinetics of Methylin.

Patients with Hepatic Impairment
Methylin has not been studied in patients with hepatic impairment. Since methylphenidate is metabolized primarily to ritalinic acid by nonmicrosomal hydrolytic esterases that are widely distributed throughout the body, hepatic impairment is expected to have minimal effect on the pharmacokinetics of Methylin.

13 NONCLINICAL TOXICOLOGY

13.1 Carcinogenesis, Mutagenesis, Impairment of Fertility

Carcinogenesis
In a lifetime carcinogenicity study carried out in B6C3F1 mice, methylphenidate caused an increase in hepatocellular adenomas and, in males only, an increase in hepatoblastomas, at a daily dose of approximately 60 mg/kg/day. This dose is approximately 5 times the maximum recommended human dose (MRHD) of 60 mg/kg given to adults on a mg/m^2 basis. Hepatoblastoma is a relatively rare rodent malignant tumor type. There was no increase in total malignant hepatic tumors. The mouse strain used is sensitive to the development of hepatic tumors, and the significance of these results to humans is unknown.

Methylphenidate did not cause any increase in tumors in a lifetime carcinogenicity study carried out in F344 rats; the highest dose used was approximately 45 mg/kg/day, which is approximately 7 times the MRHD (adults) on a mg/m^2 basis.

In a 24-week carcinogenicity study in the transgenic mouse strain p53+/-, which is sensitive to genotoxic carcinogens, there was no evidence of carcinogenicity. Male and female mice were fed diets containing the same concentration of methylphenidate as in the lifetime carcinogenicity study; the high-dose groups were exposed to 60 to 74 mg/kg/day of methylphenidate.

Mutagenesis
Methylphenidate was not mutagenic in the in vitro Ames reverse mutation assay, in the in vitro mouse lymphoma cell forward mutation assay, or in the in vitro chromosomal aberration assay using human lymphocytes. Sister chromatid exchanges and chromosome aberrations were increased, indicative of a weak clastogenic response, in an in vitro assay in cultured Chinese Hamster Ovary (CHO) cells. Methylphenidate was negative in vivo in males and females in the mouse bone marrow micronucleus assay.

Impairment of Fertility
No human data on the effect of methylphenidate on fertility are available. Methylphenidate did not impair fertility in male or female mice that were fed diets containing the drug in an 18-week continuous breeding study. The study was conducted at doses up to 160 mg/kg/day, approximately 13 times the maximum recommended human dose of 60 mg/day given to adults on a mg/m^2 basis.

16 HOW SUPPLIED/STORAGE AND HANDLING

How Supplied
Methylin oral solution is a colorless, grape flavored liquid available in the following strengths:

- 5 mg per 5 mL
  Bottles of 500 mL.................NDC 59630-750-50
- 10 mg per 5 mL
  Bottles of 500 mL.................NDC 59630-755-50

Storage and Handling
Store at 20° to 25°C (68° to 77°F) [see USP Controlled Room Temperature]. Dispense in tight container with child-resistant closure.

17 PATIENT COUNSELING INFORMATION

Advise the patient to read the FDA-approved patient labeling (Medication Guide).

Abuse, Misuse, and Addiction
Educate patients and their families about the risks of abuse, misuse, and addiction of Methylin, which can lead to overdose and death, and proper disposal of any unused drug [see Warnings and Precautions (5.1), Drug Abuse and Dependence (9.2), Overdosage (10)]. Advise patients to store Methylin in a safe place, preferably locked, and instruct patients to not give Methylin to anyone else.

Risks to Patients with Serious Cardiac Disease
Advise patients that there are potential risks to patients with serious cardiac disease, including sudden death, with Methylin use. Instruct patients to contact a healthcare provider immediately if they develop symptoms such as exertional chest pain, unexplained syncope, or other symptoms suggestive of cardiac disease [see Warnings and Precautions (5.2)].

Increased Blood Pressure and Heart Rate
Instruct patients that Methylin can elevate blood pressure and heart rate [see Warnings and Precautions (5.3)].

Psychiatric Adverse Reactions
Advise patients that Methylin, at recommended doses, can cause psychotic or manic symptoms, even in patients without prior history of psychotic symptoms or mania [see Warnings and Precautions (5.4)].

Priapism
Advise patients of the possibility of painful or prolonged penile erections (priapism). Instruct the patient to seek immediate medical attention in the event of priapism [see Warnings and Precautions (5.5)].

Circulation Problems in Fingers and Toes (Peripheral Vasculopathy, Including Raynaud’s Phenomenon)
Instruct patients about the risk of peripheral vasculopathy, including Raynaud’s phenomenon, and associated signs and symptoms: fingers or toes may feel numb, cool, painful, and/or may change color from pale, to blue, to red.

Instruct patients to report to their physician any new numbness, pain, skin color change, or sensitivity to temperature in fingers or toes. Instruct patients to call their physician immediately with any signs of unexplained wounds appearing on fingers or toes while taking Methylin. Further clinical evaluation (e.g., rheumatology referral) may be appropriate for certain patients [see Warnings and Precautions (5.6)].

Long-Term Suppression of Growth in Pediatric Patients
Advise patients that Methylin may cause slowing of growth and weight loss in pediatric patients [see Warnings and Precautions (5.7)].

Increased Intraocular Pressure (IOP) and Glaucoma
Advise patients that IOP and glaucoma may occur during treatment with Methylin [see Warnings and Precautions (5.9)].

Motor and Verbal Tics, and Worsening of Tourette’s Syndrome
Advise patients that motor and verbal tics and worsening of Tourette’s syndrome may occur during treatment with Methylin. Instruct patients to notify their healthcare provider if emergence of new tics or worsening of tics or Tourette’s syndrome occurs [see Warnings and Precautions (5.10)].

Pregnancy Exposure Registry
Inform patients that there is a pregnancy exposure registry that monitors pregnancy outcomes in patients exposed to Methylin during pregnancy [see Use in Specific Populations (8.1)].

Distributed by:
Shionogi Inc.
Florham Park, NJ 07932

Manufactured by:
SpecGx LLC
Webster Groves, MO 63119 USA

Methylin is a trademark of Mallinckrodt LLC.

MOS-PI-09
L20M21

An electronic copy of this medication guide can be obtained from www.mallinckrodt.com/Medguide/L20M31.pdf or by calling 1-800-778-7898 for alternate delivery options.

MEDICATION GUIDE

METHYLIN® (METH il in)
(methylphenidate hydrochloride)
oral solution, CII

What is the most important information I should know about METHYLIN?

METHYLIN may cause serious side effects, including:

- Abuse, misuse, and addiction. METHYLIN has a high chance for abuse and misuse and may lead to substance use problems, including addiction. Misuse and abuse of METHYLIN, other methylphenidate containing medicines, and amphetamine containing medicines, can lead to overdose and death. The risk of overdose and death is increased with higher doses of METHYLIN or when it is used in ways that are not approved, such as snorting or injection.
  - Your healthcare provider should check you or your child’s risk for abuse, misuse, and addiction before starting treatment with METHYLIN and will monitor you or your child during treatment.
  - METHYLIN may lead to physical dependence after prolonged use, even if taken as directed by your healthcare provider.
  - Do not give METHYLIN to anyone else. See “What is METHYLIN?” for more information.
  - Keep METHYLIN in a safe place and properly dispose of any unused medicine. See “How should I store METHYLIN?” for more information.
  - Tell your healthcare provider if you or your child have ever abused or been dependent on alcohol, prescription medicines, or street drugs.
- Risks for people with serious heart disease. Sudden death has happened in people who have heart defects or other serious heart disease.
  Your healthcare provider should check you or your child carefully for heart problems before starting treatment with METHYLIN. Tell your healthcare provider if you or your child have any heart problems, heart disease, or heart defects.
  Call your healthcare provider or go to the nearest hospital emergency room right away if you or your child have any signs of heart problems such as chest pain, shortness of breath, or fainting during treatment with METHYLIN.
  Your healthcare provider should check you or your child carefully for heart problems before starting treatment with METHYLIN. Tell your healthcare provider if you or your child have any heart problems, heart defects, high blood pressure, or have a family history of these problems.
  Your healthcare provider should check your or your child’s blood pressure and heart rate regularly during treatment with METHYLIN.
  Call your healthcare provider or go to the nearest hospital emergency room right away if you or your child have any signs of heart problems such as chest pain, shortness of breath, or fainting during treatment with METHYLIN.

- Mental (psychiatric) problems, including:
  - new or worse behavior and thought problems
  - new or worse bipolar illness
  - new psychotic symptoms (such as hearing voices, or seeing or believing things that are not real) or new manic symptoms
  Tell your healthcare provider about any mental problems you or your child have, or about a family history of suicide, bipolar illness, or depression.
  Call your healthcare provider right away if you or your child have any new or worsening mental symptoms or problems during treatment with METHYLIN, especially hearing voices, seeing or believing things that are not real, or new manic symptoms.

What is METHYLIN?
METHYLIN is a prescription medicine used for the treatment of Attention Deficit Hyperactivity Disorder (ADHD) in people 6 years of age and older. METHYLIN may help increase attention and decrease impulsiveness and hyperactivity in people with ADHD.
It is not known if METHYLIN is safe and effective for use in children under 6 years of age.
METHYLIN is a federally controlled substance (CII) because it contains methylphenidate that can be a target for people who abuse prescription medicines or street drugs. Keep METHYLIN in a safe place to protect it from theft. Never give your METHYLIN to anyone else, because it may cause death or harm them. Selling or giving away METHYLIN may harm others and is against the law.

Do not take METHYLIN if you or your child are:

- allergic to methylphenidate hydrochloride or any of the ingredients in METHYLIN. See the end of this Medication Guide for a complete list of ingredients in METHYLIN.
- taking, or have stopped taking within the past 14 days, a medicine called a monoamine oxidase inhibitor (MAOI).

Before taking METHYLIN tell your healthcare provider about all your medical conditions, including if you or your child:

- have heart problems, heart disease, heart defects, or high blood pressure
- have mental problems including psychosis, mania, bipolar illness, or depression, or have a family history of suicide, bipolar illness, or depression
- have circulation problems in fingers and toes
- have eye problems, including increased pressure in your eye, glaucoma, or problems with your close-up vision (farsightedness)
- have or had repeated movements or sounds (tics) or Tourette’s syndrome, or have a family history of tics or Tourette’s syndrome
- are pregnant or plan to become pregnant. It is not known if METHYLIN will harm the unborn baby.
  - There is a pregnancy registry for females who are exposed to METHYLIN during pregnancy. The purpose of the registry is to collect information about the health of females exposed to METHYLIN and their baby. If you or your child becomes pregnant during treatment with METHYLIN, talk to your healthcare provider about registering with the National Pregnancy Registry for Psychostimulants at 1-866-961-2388.
- are breastfeeding or plan to breastfeed. METHYLIN passes into breast milk. Talk to your healthcare provider about the best way to feed the baby during treatment with METHYLIN.

Tell your healthcare provider about all the medicines that you take or your child take, including prescription and over-the-counter medicines, vitamins, and herbal supplements.
METHYLIN and some medicines may interact with each other and cause serious side effects. Sometimes the doses of other medicines will need to be changed during treatment with METHYLIN. Your healthcare provider will decide whether METHYLIN can be taken with other medicines.
Especially tell your healthcare provider if you or your child take a medicine used to treat depression called a monoamine oxidase inhibitor (MAOI).
Know the medicines that you take or your child take. Keep a list of your medicines with you to show your healthcare provider and pharmacist. Do not start any new medicine during treatment with METHYLIN without talking to your healthcare provider first.

How should METHYLIN be taken?

- Take METHYLIN exactly as prescribed by your healthcare provider.
- Your healthcare provider may change the dose if needed.
- Children 6 years of age and older:
  - Take METHYLIN by mouth 2 times a day before breakfast and lunch, 30 to 45 minutes before a meal, as prescribed by your healthcare provider.
- Adults:
  - Take METHYLIN by mouth 2 or 3 times a day, 30 to 45 minutes before a meal, as prescribed by your healthcare provider.
  - For adults who have sleep problems when METHYLIN is taken late in the day, take your last dose of METHYLIN before 6 p.m.
- If you or your child take too much METHYLIN, call your healthcare provider or Poison Help Line at 1-800-222-1222 or go to the nearest hospital emergency room right away.

What are the possible side effects of METHYLIN?
METHYLIN may cause serious side effects, including:

- See “What is the most important information I should know about METHYLIN?”
- Painful and prolonged erections (priapism). Priapism has happened in males who take products that contain methylphenidate. If you or your child develop priapism, get medical help right away.
- Circulation problems in fingers and toes (peripheral vasculopathy, including Raynaud’s phenomenon).
  Signs and symptoms may include:
  - fingers or toes may feel numb, cool, painful
  - fingers or toes may change color from pale, to blue, to red

Tell your healthcare provider if you or your child have numbness, pain, skin color change, or sensitivity to temperature in the fingers or toes, or if you or your child have any signs of unexplained wounds appearing on fingers or toes during treatment with METHYLIN.

- Slowing of growth (height and weight) in children. Children should have their height and weight checked often during treatment with METHYLIN. METHYLIN treatment may be stopped if your child is not growing or gaining weight.
- Eye problems (increased pressure in the eye and glaucoma). Call your healthcare provider right away if you or your child develop changes in your vision or eye pain, swelling, or redness.
- New or worsening tics or worsening Tourette’s syndrome. Tell your healthcare provider if you or your child get any new or worsening tics or worsening Tourette’s syndrome during treatment with METHYLIN.

The most common side effects of METHYLIN include:

- increased heart rate
- headache
- anxiety
- weight loss
- dry mouth
- stomach pain
- irregular heart beat (palpitations)
- trouble sleeping
- sweating
- decreased appetite
- nausea

These are not all the possible side effects of METHYLIN.
Call your doctor for medical advice about side effects. You may report side effects to FDA at 1-800-FDA-1088.

How should I store METHYLIN?

- Store METHYLIN at room temperature between 68°F to 77°F (20°C to 25°C).
  Store METHYLIN in a safe place, like a locked cabinet.
- Protect from light and moisture.
- Dispose of remaining, unused, or expired METHYLIN by a medicine take-back program at a U.S. Drug Enforcement Administration (DEA) authorized collection site. If no take-back program or DEA authorized collector is available, mix METHYLIN with an undesirable, nontoxic substance such as dirt, cat litter, or used coffee grounds to make it less appealing to children and pets. Place the mixture in a container such as a sealed plastic bag and throw away METHYLIN in the household trash. Visit www.fda.gov/drugdisposal for additional information on disposal of unused medicines.

Keep METHYLIN and all medicines out of the reach of children.

General information about the safe and effective use of METHYLIN.
Medicines are sometimes prescribed for purposes other than those listed in a Medication Guide. Do not use METHYLIN for a condition for which it was not prescribed. Do not give METHYLIN to other people, even if they have the same symptoms. It may harm them and it is against the law. You can ask your healthcare provider or pharmacist for information about METHYLIN that is written for healthcare professionals.

What are the ingredients in METHYLIN?

Active Ingredient: methylphenidate hydrochloride USP

Inactive Ingredients: citric acid anhydrous, glycerin, N&A grape flavor, PEG 1450, and purified water

Distributed by: Shionogi Inc., Florham Park, NJ 07932

Manufactured by: SpecGx LLC, Webster Groves, MO 63119 USA

For more information go to www.methylinrx.com or call 1-800-849-9707.

This Medication Guide has been approved by the U.S. Food and Drug Administration.

Revised: 11/2023

MOS-MG-07
L20M31

PRINCIPAL DISPLAY PANEL - 5 mg per 5 mL

NDC 59630-750-50
500 mL
CII
Methylin® Oral Solution
methylphenidate HCl oral solution
5 mg per 5 mL
Rx only
PHARMACIST: Dispense the Medication Guide provided separately to each patient.
SHIONOGI INC.

L00M63

Rev 10/2018

PRINCIPAL DISPLAY PANEL - 10 mg per 5 mL

NDC 59630-755-50
500 mL
CII
Methylin® Oral Solution
methylphenidate HCl oral solution
10 mg per 5 mL
Rx only
PHARMACIST: Dispense the Medication Guide provided separately to each patient.
SHIONOGI INC.

L00M62

Rev 10/2018